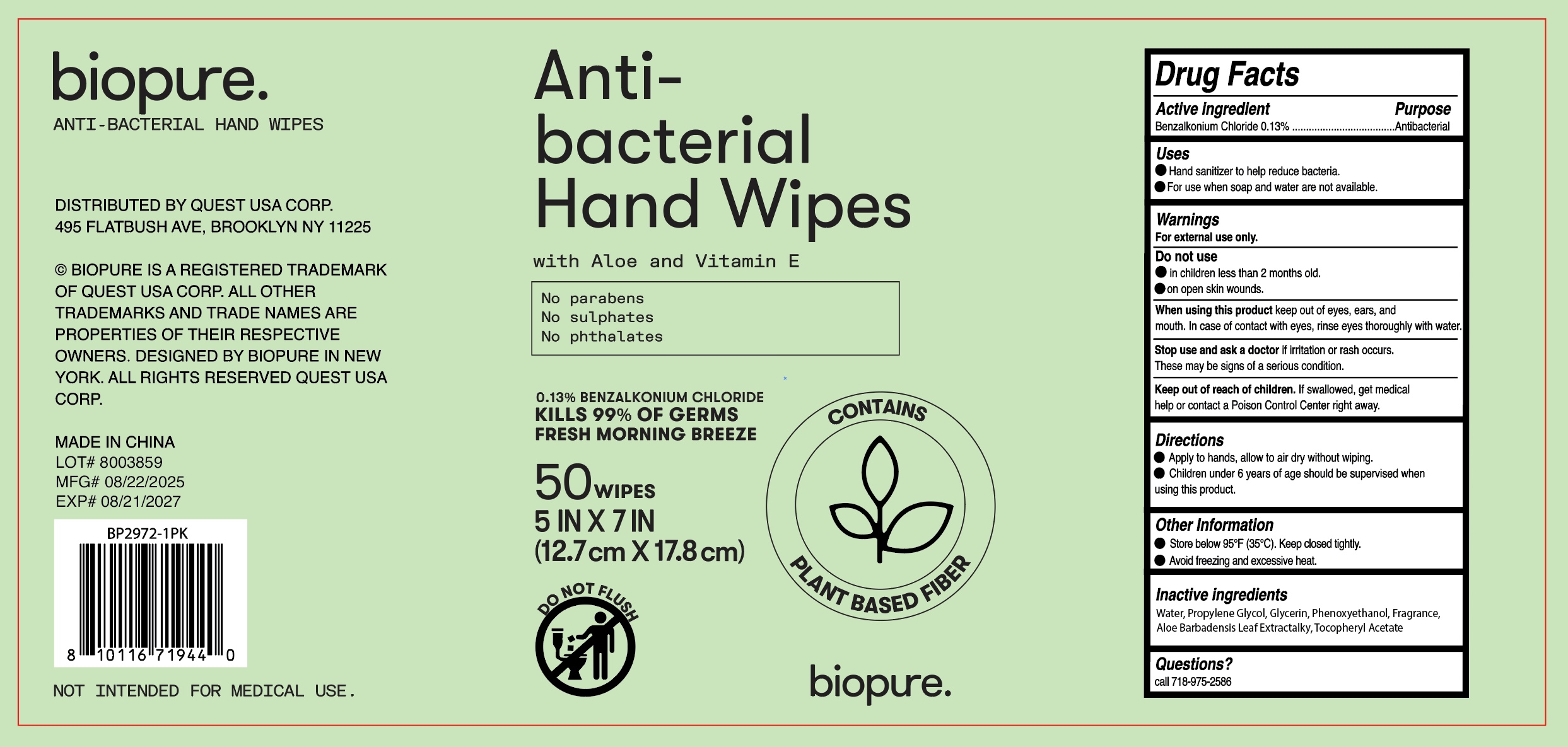 DRUG LABEL: 5OCT ANTIBACTERL HAND WIPES
NDC: 75181-011 | Form: CLOTH
Manufacturer: Jinhua Aidi Daily Chemical Co., Ltd.
Category: otc | Type: HUMAN OTC DRUG LABEL
Date: 20250901

ACTIVE INGREDIENTS: BENZALKONIUM CHLORIDE 0.13 g/100 g
INACTIVE INGREDIENTS: .ALPHA.-TOCOPHEROL ACETATE, D-; PROPYLENE GLYCOL; ALOE BARBADENSIS LEAF; GLYCERIN; PHENOXYETHANOL; WATER

5OCT ANTIBACTERL HAND WIPES
75181-011-01

Active Ingredient(s)

Benzalkonium Chloride 0.13%

Purpose

Antimicrobial

Use

Hand sanitizer to help reduce bacteria.
For use when soap and water are not available.

Warnings

For external use only.

Do not use

in children less than 2 months old.

on open skin wounds.

When using this product
keep out of eyes, ears, and mouth. In case of contact with eyes, rinse eyes thoroughly with water.

Stop use and ask a doctor if irritation or rash occurs, These may be signs of a serious condition.

Keep out of reach of children. lf swallowed, get medical help or contact a Poison Control Center right away.

Directions

Apply to hands, allow to air dry without wiping.
Children under 6 years of age should be supervised when using this product.

Other information

Store below 95°F (35°C). Keep closed tightly.
Avoid freezing and excessive heat.

Inactive ingredients

Water, Propylene Glycol, Glycerin, Phenoxyethanol, Fragrance, Aloe Barbadensis Leaf Extractalky,Tocopheryl Acetate

Package Label - Principal Display Panel

50 wipes in 1 bottle NDC: 75181-011-01